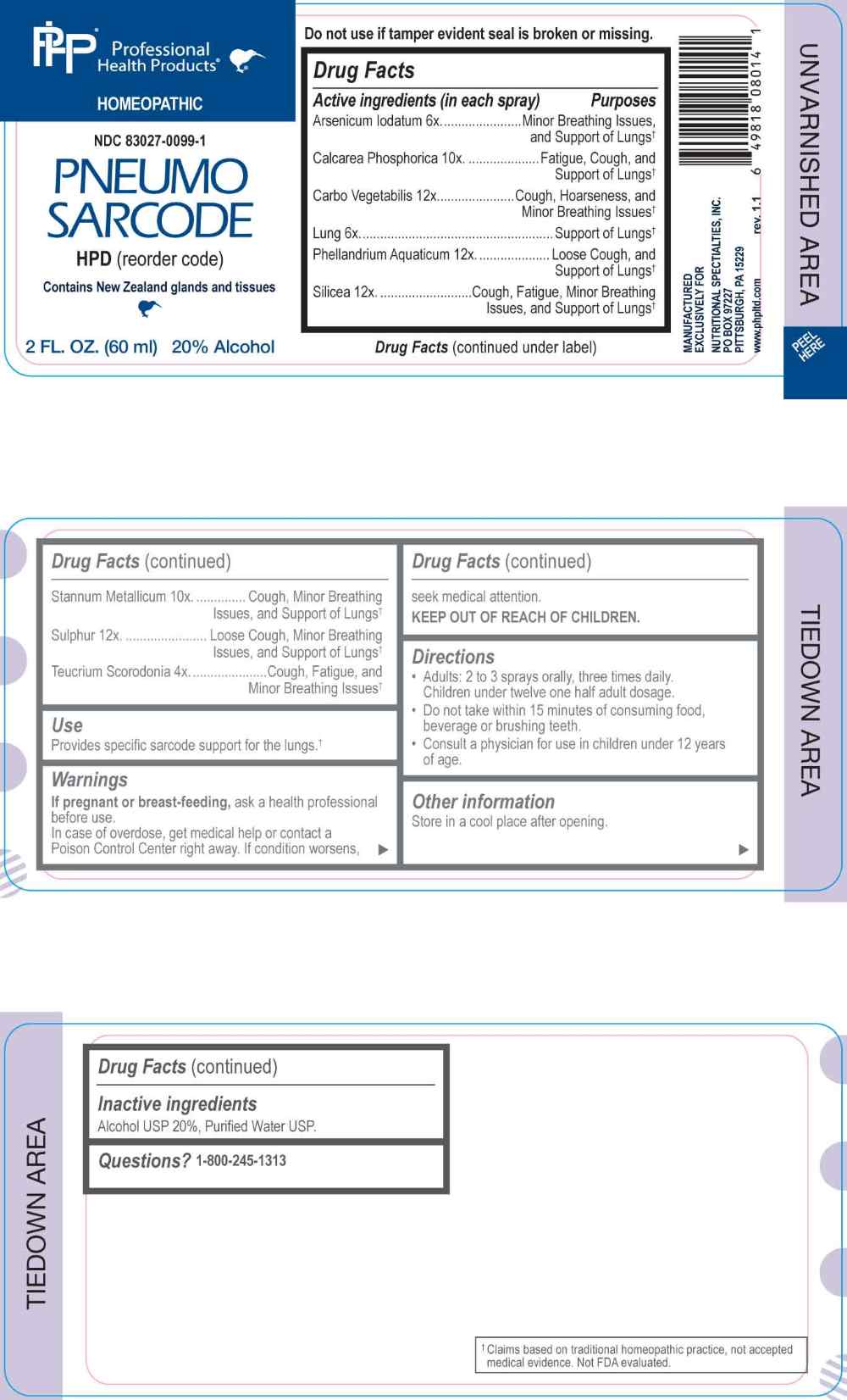 DRUG LABEL: Pneumo Sarcode
NDC: 83027-0099 | Form: SPRAY
Manufacturer: Nutritional Specialties, Inc.
Category: homeopathic | Type: HUMAN OTC DRUG LABEL
Date: 20251120

ACTIVE INGREDIENTS: TEUCRIUM SCORODONIA FLOWERING TOP 4 [hp_X]/1 mL; ARSENIC TRIIODIDE 6 [hp_X]/1 mL; BEEF LUNG 6 [hp_X]/1 mL; TRIBASIC CALCIUM PHOSPHATE 10 [hp_X]/1 mL; TIN 10 [hp_X]/1 mL; ACTIVATED CHARCOAL 12 [hp_X]/1 mL; OENANTHE AQUATICA FRUIT 12 [hp_X]/1 mL; SILICON DIOXIDE 12 [hp_X]/1 mL; SULFUR 12 [hp_X]/1 mL
INACTIVE INGREDIENTS: WATER; ALCOHOL

DRUG FACTS:

ACTIVE INGREDIENTS:

Arsenicum Iodatum 6X, Calcarea Phosphorica 10X, Carbo Vegetabilis 12X, Lung 6X, Phellandrium Aquaticum 12X, Silicea 12X, Stannum Metallicum 10X, Sulphur 12X, Teucrium Scorodonia 4X.

PURPOSE:

Arsenicum Iodatum – Minor Breathing Issues, and Support of Lungs,† Calcarea Phosphorica – Fatigue, Cough, and Support of Lungs,† Carbo Vegetabilis – Cough, Hoarseness, and Minor Breathing Issues,† Lung – Support of Lungs,† Phellandrium Aquaticum – Loose Cough, and Support of Lungs,† Silicea – Cough, Fatigue, Minor Breathing Issues, and Support of Lungs,† Stannum Metallicum – Cough, Fatigue, Minor Breathing Issues, and Support of Lungs,† Sulphur – Loose Cough, Minor Breathing Issues, and Support of Lungs,† Teucrium Scorodonia – Cough, Fatigue, and Minor Breathing Issues†

†Claims based on traditional homeopathic practice, not accepted medical evidence. Not FDA evaluated.

USE:

Provides specific sarcode support for the lungs.†
†Claims based on traditional homeopathic practice, not accepted medical evidence. Not FDA evaluated.

WARNINGS:

If pregnant or breast-feeding, ask a health professional before use.

In case of overdose, get medical help or contact a Poison Control Center right away.

If condition worsens, seek medical attention.

KEEP OUT OF REACH OF CHILDREN

Do not use if tamper evident seal is broken or missing.

Store in a cool place after opening

KEEP OUT OF REACH OF CHILDREN:

In case of overdose, get medical help or contact a Poison Control Center right away.

DIRECTIONS:

• Adults: 2 to 3 sprays orally, three times daily. Children under twelve one half adult dosage.

• Do not take within 15 minutes of consuming food, beverage or brushing teeth.

Consult a physician for use in children under 12 years of age.

INACTIVE INGREDIENTS:

Alcohol USP 20%, Purified Water USP.

QUESTIONS:

MANUFACTURED EXCLUSIVELY FOR

NUTRITIONAL SPECIALTIES, INC.

PO BOX 97227

PITTSBURG, PA 15229

www.phpltd.com

1-800-245-1313

PACKAGE LABEL DISPLAY:

Professional

Health Products

HOMEOPATHIC

NDC 83027-0099-1

PNEUMO SARCODE

2 FL. OZ (60 ml)

b